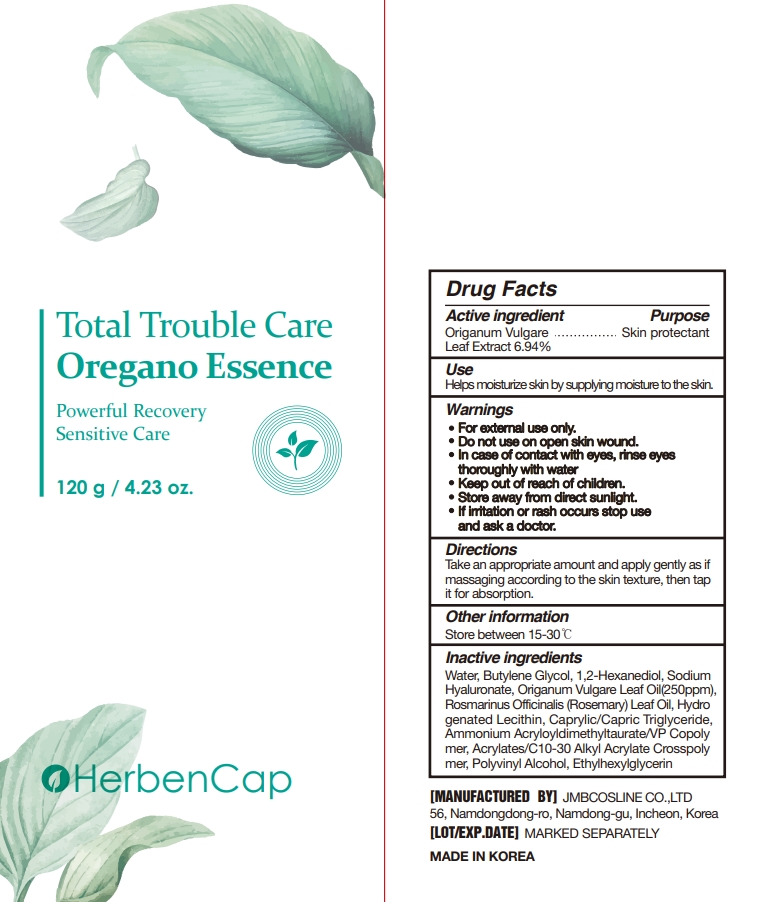 DRUG LABEL: Oregano-Lotion
NDC: 90028-202 | Form: LOTION
Manufacturer: JMB COSLINE CO.,LTD
Category: otc | Type: HUMAN OTC DRUG LABEL
Date: 20201113

ACTIVE INGREDIENTS: OREGANO 5.74 g/100 g
INACTIVE INGREDIENTS: MADECASSOSIDE; XYLITYLGLUCOSIDE; ANHYDROXYLITOL; OREGANO LEAF OIL; ROSEMARY OIL; MACADAMIA OIL; SHEA BUTTER; CETEARYL OLIVATE; SUCROSE STEARATE; XYLITOL; GLYCERYL MONOSTEARATE; TREHALOSE; TROMETHAMINE; POLYVINYL ALCOHOL, UNSPECIFIED; PROPANEDIOL; ASIATIC ACID; HYDROGENATED POLYBUTENE (1300 MW); CENTELLA ASIATICA; ASIATICOSIDE; HYDROGENATED SOYBEAN LECITHIN; CORIANDER OIL; LIMONENE, (+)-; CARBOMER INTERPOLYMER TYPE A (55000 CPS); CAPRYLYL GLYCOL; PANTHENOL; ALLANTOIN; BERGAMOT OIL; LINALOOL, (+/-)-; 1,2-HEXANEDIOL; GLYCERIN; CETOSTEARYL ALCOHOL; BUTYLENE GLYCOL; STAR ANISE FRUIT; MADECASSIC ACID; MEDIUM-CHAIN TRIGLYCERIDES; HYALURONATE SODIUM; BETAINE; SORBITAN OLIVATE; EDETATE DISODIUM ANHYDROUS; ETHYLHEXYLGLYCERIN

90028-202

Active ingredient

Origanum Vulgare Leaf Extract 5.74%

Purpose

Skin protectant

Use

Helps to make your skin energized and lively.

Warnings

- For external use only.
- Do not use on open skin wound.
- In case of contact with eyes, rinse eyes thoroughly with water
- Store away from direct sunlight.

Warnings

- Keep out of reach of children.

Warnings

- If irritation or rash occurs stop use and ask a doctor.

Directions

Take an appropriate amount and apply gently as if massaging according to the skin texture, then tap it for absorption.

Other information

Store between 15-30℃

Inactive ingredients

Water, Butylene Glycol, Hydrogenated Polyisobu tene, Glycerin, 1,2-Hexanediol, Polyglyceryl-3 Me thylglucose Distearate, Cetearyl Alcohol, Sodium Hyaluronate, Centella Asiatica Extract, Lactobacillus/ Soybean Ferment Extract, Lactobacillus/Rice Fer ment, Lactobacillus/Panax Ginseng Root Ferment Filtrate, Saccharomyces/Coix Lacryma-Jobi Mayuen Seed Ferment Filtrate, Saccharomyces/Potato Extract Ferment Filtrate, Illicium Verum (Anise) Fruit Extract, Xylitylglucoside, Anhydroxylitol, Xylitol, Asiaticoside, Madecassic Acid, Asiatic Acid, Made cassoside, Origanum Vulgare Leaf Oil(250ppm), Rosmarinus Officinalis (Rosemary) Leaf Oil, Maca damia Ternifolia Seed Oil, Butyrospermum Parkii (Shea) Butter, Glycosaminoglycans, Glyceryl Stea rate, Betaine, Cetearyl Olivate, Sorbitan Olivate, Sucrose Stearate, Simethicone, Acrylates/C10-30 Alkyl Acrylate Crosspolymer, Caprylic/Capric Trigly ceride, Caprylyl Glycol, Trehalose, Tromethamine, Panthenol, Polyvinyl Alcohol, Propanediol, Hydro genated Lecithin, Hydrogenated Phosphatidylcho line, Allantoin, Disodium EDTA, Ethylhexylglycerin, Citrus Aurantium Bergamia (Bergamot) Fruit Oil, Coriandrum Sativum (Coriander) Fruit Oil